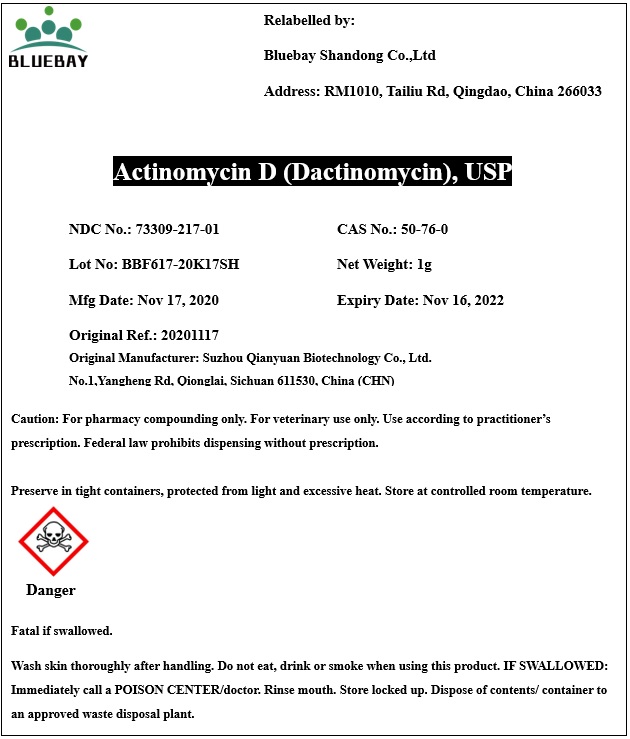 DRUG LABEL: Actinomycin D (Dactinomycin)
NDC: 73309-217 | Form: POWDER
Manufacturer: BLUEBAY SHANDONG CO.,LTD
Category: other | Type: BULK INGREDIENT
Date: 20201231

ACTIVE INGREDIENTS: DACTINOMYCIN 1 g/1 g

Actinomycin D (Dactinomycin)